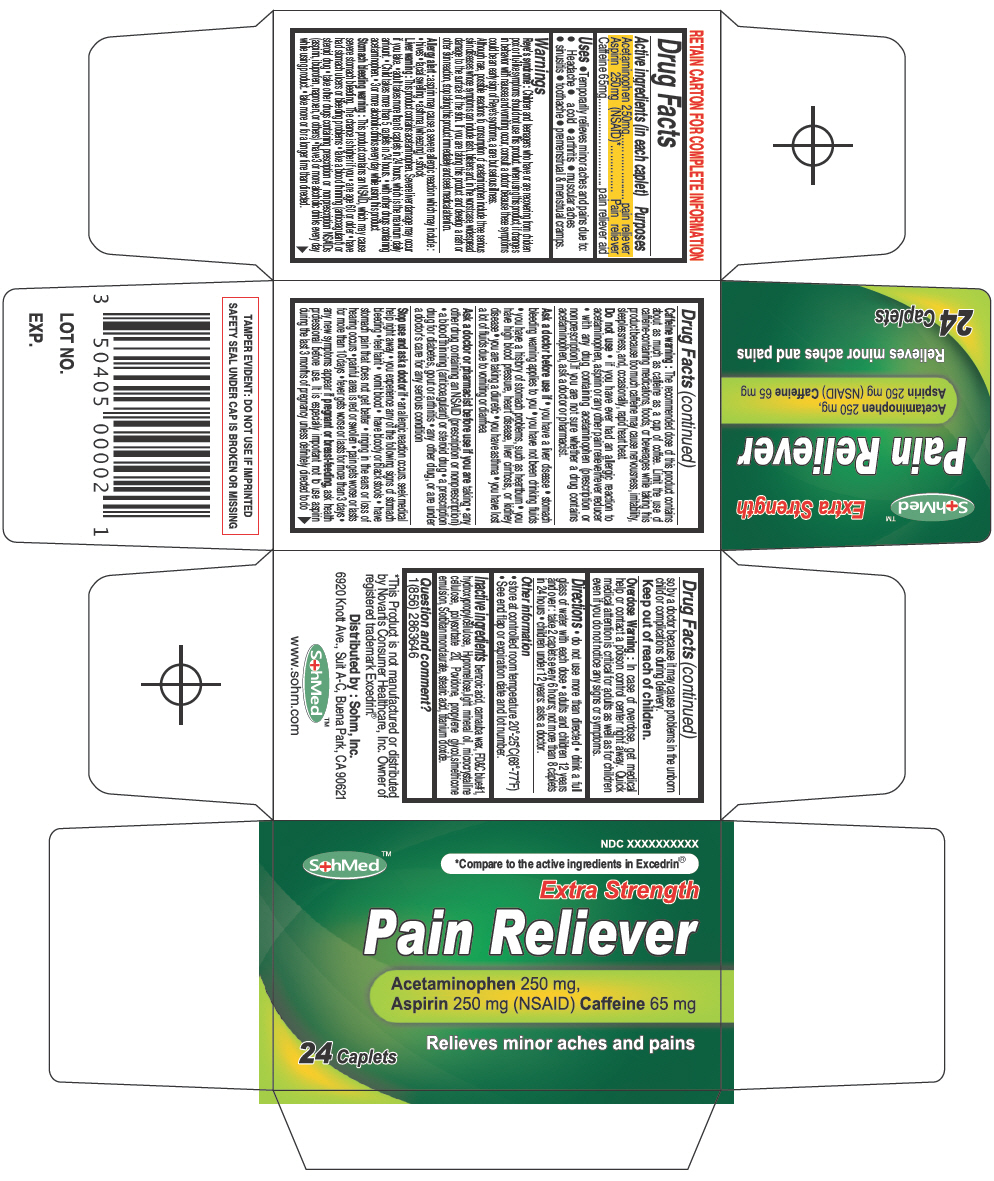 DRUG LABEL: SohMed Pain Reliever
NDC: 50405-008 | Form: TABLET
Manufacturer: SOHM Inc.
Category: otc | Type: HUMAN OTC DRUG LABEL
Date: 20130822

ACTIVE INGREDIENTS: Acetaminophen 250 mg/1 1; Aspirin 250 mg/1 1; Caffeine 65 mg/1 1
INACTIVE INGREDIENTS: CARNAUBA WAX; BENZOIC ACID; HYDROXYPROPYL CELLULOSE (TYPE H); FD&C BLUE NO. 1; HYPROMELLOSES; LIGHT MINERAL OIL; CELLULOSE, MICROCRYSTALLINE; POLYSORBATE 20; POVIDONES; PROPYLENE GLYCOL; DIMETHICONE; SORBITAN MONOLAURATE; STEARIC ACID; TITANIUM DIOXIDE

SohMed™ Pain Reliever

Drug Facts

ACTIVE INGREDIENT

PURPOSE

Active ingredients (in each caplet) | Purposes
Acetaminophen 250mg | pain reliever
Aspirin 250mg (NSAID) [This Product is not manufactured or distributed by Novartis Consumer Healthcare, Inc. Owner of registered trademark Excedrin®.] | Pain reliever
Caffeine 65mg | pain reliever aid

Uses

- Temporarily relieves minor aches and pains due to:
  - Headache
  - a cold
  - arthritis
  - muscular aches
  - sinusitis
  - toothache
  - premenstrual & menstrual cramps.

Warnings

Reye's syndrome

Children and teenagers who have or are recovering from chicken pox or flu-like symptoms should not use this product. when using this product, if changes in behavior with nausea and vomiting occur, consult a doctor because these symptoms could be an early sign of Reye's syndrome, a rare but serious illness.

Although rare, possible reactions to consumption of acetaminophen include three serious skin diseases whose symptoms can include rash, blisters and, in the worst case, widespread damage to the surface of the skin. If you are taking this product and develop a rash or other skin reaction, stop taking this product immediately and seek medical attention.

Allergy alert

aspirin may cause a severe allergic reaction which may include :

- hives
- facial swelling
- asthma (wheezing)
- shock

Liver warning

This product contains acetaminophen. Severe liver damage may occur if you take.

- adult takes more than 8 caplets in 24 hours, which is the maximum daily amount.
- Child takes more than 5 caplets in 24 hours.
- with other drugs containing acetaminophen.
- 3 or more alcoholic drinks every day while using this product.

Stomach bleeding warning

This product contains an NSAID, which may cause severe stomach bleeding. The chance is higher if you

- are age 60 or older
- have had stomach ulcers or bleeding problems
- take a blood thinning (anticoagulant) or steroid drug
- take other drugs containing prescription or nonprescription NSAIDs (aspirin, ibuprofen, naproxen, or others)
- have 3 or more alcoholic drinks every day while using product.
- take more or for a longer time than directed.

Caffeine warning

The recommended dose of this product contains about as much as caffeine as a cup of coffee. Limit the use of caffeine-containing medications, foods, or beverages while taking this product because too much caffeine may cause nervousness, irritability, sleeplessness, and, occasionally, rapid heart beat.

Do not use

- if you have ever had an allergic reaction to acetaminophen, aspirin or any other pain reliever/fever reducer
- with any drug containing acetaminophen (prescription or nonprescription).If you are not sure whether a drug contains acetaminophen, ask a doctor or pharmacist.

Ask a doctor before use if

- you have a liver disease
- stomach bleeding warning applies to you
- you have not been drinking fluids
- you have a history of stomach problems, such as heartburn
- you have high blood pressure, heart disease, liver cirrhosis, or kidney disease
- you are taking a diuretic
- you have asthma
- you have lost a lot of fluids due to vomiting or diarrhea

Ask a doctor or pharmacist before use if you are taking

- any other drug containing an NSAID (prescription or nonprescription)
- a blood thinning (anticoagulant) or steroid drug
- a prescription drug for diabetes, gout or arthritis
- any other drug, or are under a doctor's care for any serious condition

Stop use and ask a doctor if

- an allergic reaction occurs. seek medical help right away
- you experience any of the following signs of stomach bleeding
- feel faint
- vomit blood
- have bloody or black stools
- have stomach pain that does not get better
- ringing in the ears or loss of hearing occurs
- painful area is red or swollen
- pain gets worse or lasts for more than 10 days
- fever gets worse or lasts for more than 3 days

PREGNANCY OR BREAST FEEDING

- any new symptoms appear if pregnant or breast-feeding, ask health professional before use. It is especially important not to use aspirin during the last 3 months of pregnancy unless definitely directed to do so by a doctor because it may cause problems in the unborn child or complications during delivery.

Keep out of reach of children.

Overdose Warning

In case of overdose, get medical help or contact a poison control center right away. Quick medical attention is critical for adults as well as for children even if you do not notice any signs or symptoms.

Directions

- do not use more than directed
- drink a full glass of water with each dose
- adults and children 12 years and over : take 2 caplets every 6 hours; not more than 8 caplets in 24 hours
- children under 12 years: asks a doctor.

Other information

- store at controlled room temperature 20°-25°C(68°-77°F)
- See end flap or expiration date and lot number.

Inactive ingredients

benzoic acid, carnauba wax, FD&C blue#1, hydroxypropylcellulose, Hypromellose,light mineral oil, microcrystalline cellulose, polysorbate 20, Povidone, propylene glycol,simethicone emulsion, Sorbitan monolaurate, stearic acid, titanium dioxide.

Question and comment?

1(856) 2863646

Distributed by : Sohm, Inc.
6920 Knott Ave., Suit A-C, Buena Park, CA 90621

PRINCIPAL DISPLAY PANEL - 24 Caplet Bottle Carton

SohMed™

NDC XXXXXXXXXX

*Compare to the active ingredients in Excedrin®

Extra Strength
Pain Reliever

Acetaminophen 250 mg,
Aspirin 250 mg (NSAID) Caffeine 65 mg

Relieves minor aches and pains

24 Caplets